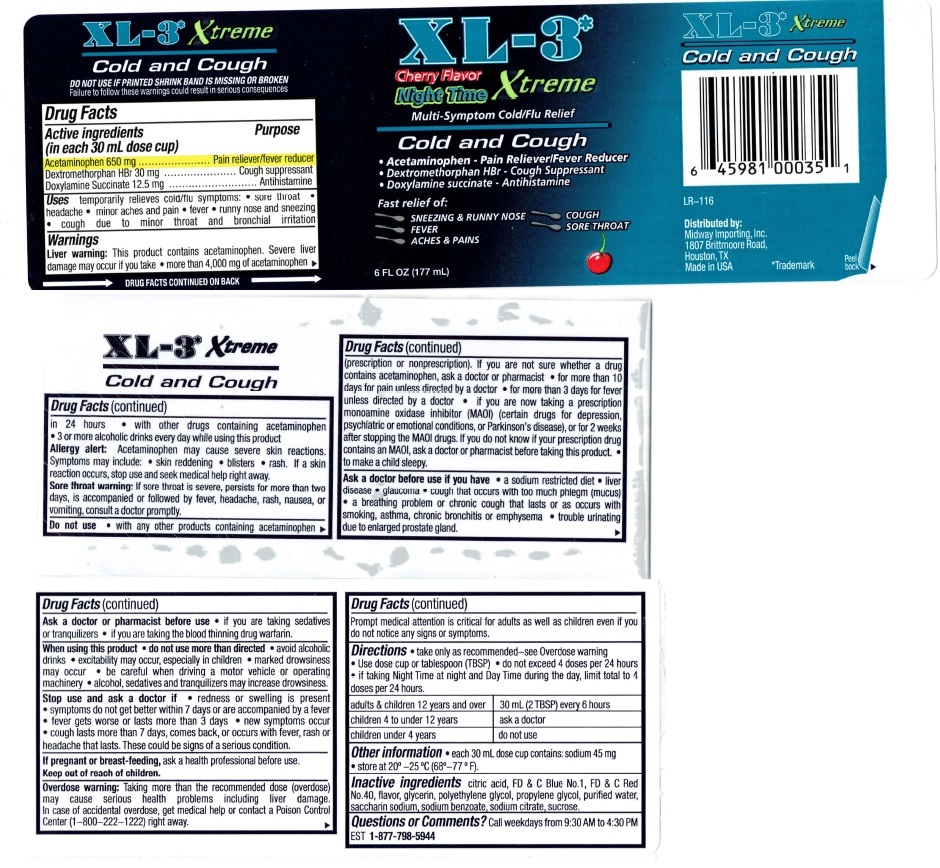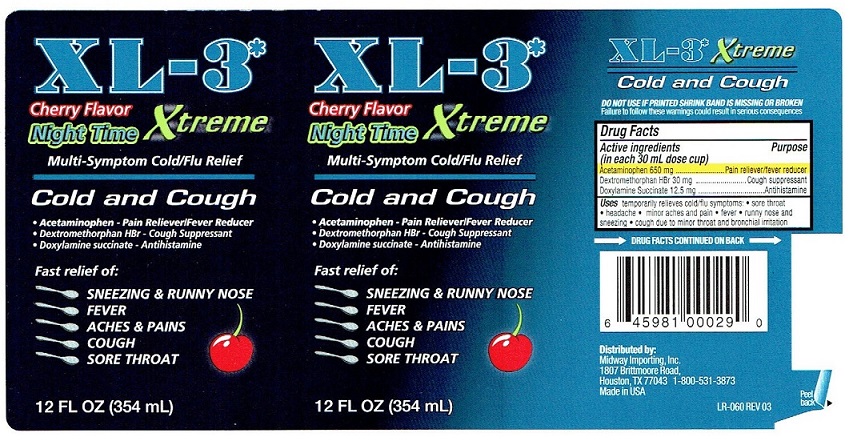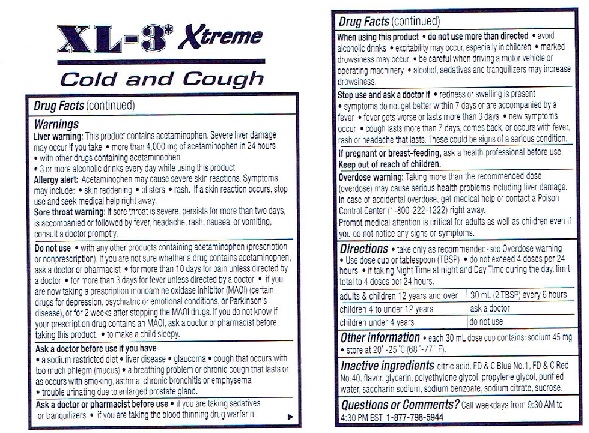 DRUG LABEL: XL-3 Xtreme
NDC: 76281-305 | Form: LIQUID
Manufacturer: AptaPharma Inc.
Category: otc | Type: HUMAN OTC DRUG LABEL
Date: 20231230

ACTIVE INGREDIENTS: Acetaminophen 650 mg/30 mL; DEXTROMETHORPHAN HYDROBROMIDE 30 mg/30 mL; DOXYLAMINE SUCCINATE 12.5 mg/30 mL
INACTIVE INGREDIENTS: CITRIC ACID MONOHYDRATE; FD&C BLUE NO. 1; FD&C RED NO. 40; GLYCERIN; POLYETHYLENE GLYCOL, UNSPECIFIED; PROPYLENE GLYCOL; WATER; SACCHARIN SODIUM; SODIUM BENZOATE; SODIUM CITRATE; SUCROSE

XL-3* Xtreme Night Time Cold and Cough

Drug Facts

Active Ingredients

(in each 30 mL dose cup)
Acetaminophen 650 mgr
Dextromethorphan HBr 30 mg
Doxylamine Succinate 12.5 mg

Purpose

Pain reliever/fever reducer
Cough suppressant
Antihistamine

Use

temporarily relieves cold/flu symptoms: • sore throat
headache • minor aches and pain • fever • runny nose and
sneezing • cough due to minor throat and bronchial irritation

Warnings

Liver warning: This product contains acetaminophen. Severe liver damage may occur if you take • more than 4,000 mg of acetaminophen in 24 hours • with other drugs containing acetaminophen • 3 or more alcoholic drinks every day while using this product
Allergy alert: Acetaminophen may cause severe skin reactions. Symptoms
may include: • skin reddening • blisters • rash. If a skin reaction occurs,
stop use and seek medical help right away.
Sore throat warning: If sore throat is severe, persists for more than two days, is accompanied or followed by fever, headache, rash, nausea, or vomiting, consult a doctor promptly.

Do not use

• with any other products containing acetaminophen (prescription or nonprescription). lf you are not sure whether a drug contains acetaminophen, ask a doctor or pharmacist • for more than10 days for pain unless directed by a doctor • for more than 3 days for fever unless directed by a doctor • if you are now taking a prescription monoamine oxidase inhibitor (MAOI) (certain drugs for depression, psychiatric or emotional conditions, or Parkinson’s disease), or for 2 weeks after stopping the MAOI drugs. If you do not know if your prescription drug contains an MAOI, ask a doctor or pharmacist before taking this product.
• to make a child sleepy.

Ask a doctor before use if you have

• a sodium restricted diet • liver disease • glaucoma • cough that occurs with too much phlegm (mucus) • a breathing problem or chronic cough that lasts or as occurs with smoking, asthma, chronic bronchitis or emphysema
• trouble urinating due to enlarged prostate gland.

Ask a doctor or pharmacist before use

• if you are taking sedatives or tranquilizers • if you are taking the blood thinning drug warfarin.

When using this product

• do not use more than directed • avoid alcoholic drinks
• excitability may occur, especially in children • marked
drowsiness may occur • be careful when driving a motor vehicle or
operating machinery • alcohol, sedatives and tranquilizers may increase
drowsiness.

Stop use and ask a doctor if

• redness or swelling is present
• symptoms do not get better within 7 days or are accompanied by a fever
• fever gets worse or lasts more than 3 days • new symptoms occur
• cough lasts more than 7 days, comes back, or occurs with fever, rash or headache that lasts. These could be signs of a serious condition.

If pregnant or breast-feeding,

ask a health professional before use.

Keep out of reach of children.

Overdose warning:

Taking more than the recommended dose
(overdose) may cause serious health problems including liver damage.
In case of accidental overdose, get medical help or contact a Poison
Control Center (1-800-222-1222) right away.
Prompt medical attention is critical for adults as well as children even if
you do not notice any signs or symptoms.

Directions

• take only as recommended-see Overdose warning
• Use dose cup or tablespoon (TBSP) • do not exceed 4 doses per 24 hours • if taking Night Time at night and Day Time during the day, limit total to 4 doses per 24 hours.

adults & children 12 years and over 30 mL (2 TBSP) every 6 hours
children 4 to under 12 years ask a doctor
children under 4 years do not use

Other information

• each 30 mL dose cup contains: sodium 45 mg
• store at 20°-25°C (68°-77° F).

Inactive ingredients

citric acid, FD & C Blue No.1, FD & C Red No. 40, flavor, glycerin, polyethylene glycol, propylene glycol, purified water, saccharin sodium, sodium benzoate, sodium citrate, sucrose.

Questions or Comments? Call weekdays from 9:30 AM to 4:30 PM EST
1-877-798-5944

XL-3 Xtreme Night Time Cold and Cough

XL-3* Xtreme
Cherry Flavor
Night Time

Multi-Symptom Cold/Flu relief

Cold and Cough
• Acetaminophen - Pain Reliever/Fever Reducer
• Dextromethorphan HBr - Cough Suppressant
• Doxylamine succinate - Antihistamine

Fast Relief of:
SNEEZING & RUNNY NOSE
FEVER
ACHES & PAINS
COUGH
SORE THROAT

12 FL OZ (354 mL)

XL-3* Xtreme
Cherry Flavor
Night Time

Multi-Symptom Cold/Flu relief

Cold and Cough
• Acetaminophen - Pain Reliever/Fever Reducer
• Dextromethorphan HBr - Cough Suppressant
• Doxylamine succinate - Antihistamine

Fast Relief of:
SNEEZING & RUNNY NOSE
FEVER
ACHES & PAINS
COUGH
SORE THROAT

12 FL OZ (354 mL)

XL-3* Xtreme

Cold and Cough

DO NOT USE IF PRINTED SHRINK BAND IS MISSING OR BROKEN
Failure to follow these warnings could result in serious consequences

Drug Facts

Active ingredients Purpose
(in each 30 mL dose cup)
Acetaminophen 650 mg ........................ Pain reliever/fever reducer
Dextromethorphan HBr 30 mg ..........................Cough suppressant
Doxylamine Succinate 12.5 mg ...................................Antihistamine

Uses temporarily relieves cold/flu symptoms: • sore throat
headache • minor aches and pain • fever • runny nose and
sneezing • cough due to minor throat and bronchial irritation

→ DRUG FACTS CONTINUED ON BACK →

Distributed by:
Midway Importing, Inc.
1807 Brittmoore Road,
Houston, TX 77043 1-800-531-3873
Made in USA
Peel
LR-060 REV 03 back ►

XL-3* Xtreme

Cold and Cough

Drug Facts (continued)

Warnings
Liver warning: This product contains acetaminophen. Severe liver damage may occur if you take • more than 4,000 mg of acetaminophen in 24 hours • with other drugs containing acetaminophen • 3 or more alcoholic drinks every day while using this product
Allergy alert: Acetaminophen may cause severe skin reactions. Symptoms
may include: • skin reddening • blisters • rash. If a skin reaction occurs,
stop use and seek medical help right away.
Sore throat warning: If sore throat is severe, persists for more than two days, is accompanied or followed by fever, headache, rash, nausea, or vomiting, consult a doctor promptly.

Do not use • with any other products containing acetaminophen (prescription or nonprescription). lf you are not sure whether a drug contains acetaminophen, ask a doctor or pharmacist • for more than10 days for pain unless directed by a doctor • for more than 3 days for fever unless directed by a doctor • if you are now taking a prescription monoamine oxidase inhibitor (MAOI) (certain drugs for depression, psychiatric or emotional conditions, or Parkinson’s disease), or for 2 weeks after stopping the MAOI drugs. If you do not know if your prescription drug contains an MAOI, ask a doctor or pharmacist before taking this product.
• to make a child sleepy.

Ask a doctor before use if you have
• a sodium restricted diet • liver disease • glaucoma • cough that occurs with too much phlegm (mucus) • a breathing problem or chronic cough that lasts or as occurs with smoking, asthma, chronic bronchitis or emphysema
• trouble urinating due to enlarged prostate gland.

Ask a doctor or pharmacist before use • if you are taking sedatives or tranquilizers • if you are taking the blood thinning drug warfarin. ►

Drug Facts (continued)

When using this product • do not use more than directed • avoid
alcoholic drinks • excitability may occur, especially in children • marked
drowsiness may occur • be careful when driving a motor vehicle or
operating machinery • alcohol, sedatives and tranquilizers may increase
drowsiness.

Stop use and ask a doctor if • redness or swelling is present
• symptoms do not get better within 7 days or are accompanied by a fever
• fever gets worse or lasts more than 3 days • new symptoms occur
• cough lasts more than 7 days, comes back, or occurs with fever, rash or headache that lasts. These could be signs of a serious condition.

If pregnant or breast-feeding, ask a health professional before use.
Keep out of reach of children.

Overdose warning: Taking more than the recommended dose
(overdose) may cause serious health problems including liver damage.
In case of accidental overdose, get medical help or contact a Poison
Control Center (1-800-222-1222) right away.
Prompt medical attention is critical for adults as well as children even if
you do not notice any signs or symptoms.

Directions • take only as recommended-see Overdose warning
• Use dose cup or tablespoon (TBSP) • do not exceed 4 doses per 24 hours • if taking Night Time at night and Day Time during the day, limit total to 4 doses per 24 hours.
adults & children 12 years and over 30 mL (2 TBSP) every 6 hours
children 4 to under 12 years ask a doctor
children under 4 years do not use

Other information • each 30 mL dose cup contains: sodium 45 mg
• store at 20°-25°C (68°-77° F).

Inactive ingredients citric acid, FD & C Blue No.1, FD & C Red No. 40, flavor, glycerin, polyethylene glycol, propylene glycol, purified water, saccharin sodium, sodium benzoate, sodium citrate, sucrose.

Questions or Comments? Call weekdays from 9:30 AM to 4:30 PM EST
1-877-798-5944

XL-3* Xtreme
Cherry Flavor
Night Time

Multi-Symptom Cold/Flu relief

Cold and Cough
• Acetaminophen - Pain Reliever/Fever Reducer
• Dextromethorphan HBr - Cough Suppressant
• Doxylamine succinate - Antihistamine

Fast Relief of:
SNEEZING & RUNNY NOSE
FEVER
ACHES & PAINS
COUGH
SORE THROAT

6 FL OZ (177 mL)

res